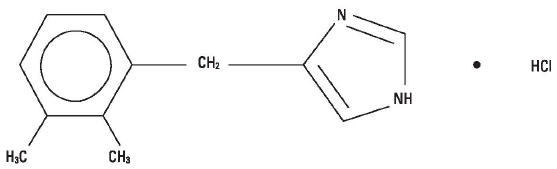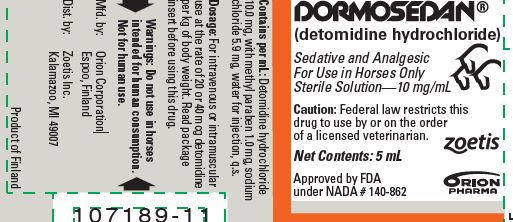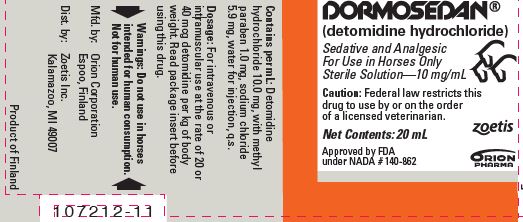 DRUG LABEL: Dormosedan
NDC: 54771-6290 | Form: SOLUTION
Manufacturer: Zoetis Inc.
Category: animal | Type: PRESCRIPTION ANIMAL DRUG LABEL
Date: 20220913

ACTIVE INGREDIENTS: DETOMIDINE HYDROCHLORIDE 10 mg/1 mL
INACTIVE INGREDIENTS: METHYLPARABEN 1 mg/1 mL; SODIUM CHLORIDE 5.9 mg/1 mL; WATER

DORMOSEDAN®
(detomidine hydrochloride)

Sedative and Analgesic For Use in Horses Only

Sterile Solution
10mg/mL

CAUTION

Federal law restricts this drug to use by or on the order of a licensed veterinarian.

DESCRIPTION

Dormosedan® is a synthetic alpha-2 adrenoreceptor agonist with sedative and analgesic properties. The chemical name is 1H imidazole, 4-[(2,3-dimethylphenyl) methyl]- hydrochloride and the generic name is detomidine hydrochloride. It is a white, crystalline, water-soluble substance having a molecular weight of 222.7. The molecular formula is C12H14N2∙HCl.

CHEMICAL STRUCTURE:

Each mL of Dormosedan® contains 10.0 mg detomidine hydrochloride, 1.0 mg methyl paraben, 5.9 mg sodium chloride, and water for injection, q.s.

CLINICAL PHARMACOLOGY

Dormosedan®, a non-narcotic sedative and analgesic, is a potent α2-adrenoreceptor agonist which produces sedation and superficial and visceral analgesia which is dose dependent in its depth and duration. Profound lethargy and a characteristic lowering of the head with reduced sensitivity to environmental stimuli (sounds, etc.) are seen with detomidine. A short period of incoordination is characteristically followed by immobility and a firm stance with front legs well spread. The analgesic effect is most readily seen as an increase in the pain threshold at the body surface. Sensitivity to touch is little affected and in some cases may actually be enhanced.

With detomidine administration, heart rate is markedly decreased, blood pressure is initially elevated, and then a steady decline to normal is seen. A transient change in the conductivity of the cardiac muscle may occur, as evidenced by partial atrioventricular (AV) and sinoauricular (SA) blocks. This change in the conductivity of the cardiac muscle may be prevented by IV administration of atropine at 0.02 mg/kg of body weight.

No effect on blood clotting time or other hematological parameters was encountered at dosages of 20 or 40 mcg/kg of body weight. Respiratory responses include an initial slowing of respiration within a few seconds to 1–2 minutes after administration, increasing to normal within 5 minutes. An initial decrease in tidal volume is followed by an increase.

INDICATIONS

Dormosedan® is indicated for use as a sedative and analgesic to facilitate minor surgical and diagnostic procedures in mature horses and yearlings. It has been used successfully for the following: to calm fractious horses, to provide relief from abdominal pain, to facilitate bronchoscopy, bronchoalveolar lavage, nasogastric intubation, nonreproductive rectal palpations, suturing of skin lacerations, and castrations. Additionally, an approved, local infiltration anesthetic is indicated for castration.

CONTRAINDICATIONS

Dormosedan® should not be used in horses with pre-existing AV or SA block, with severe coronary insufficiency, cerebrovascular disease, respiratory disease, or chronic renal failure. Intravenous potentiated sulfonamides should not be used in anesthetized or sedated horses as potentially fatal dysrhythmias may occur.

Information on the possible effects of detomidine hydrochloride in breeding horses is limited to uncontrolled clinical reports; therefore, this drug is not recommended for use in breeding animals.

WARNINGS

Do not use in horses intended for human consumption. Not for human use. Keep out of reach of children.

HUMAN SAFETY INFORMATION

Care should be taken to assure that detomidine hydrochloride is not inadvertently ingested as safety studies have indicated that the drug is well absorbed when administered orally. Standard ocular irritation tests in rabbits using the proposed market formulation have shown detomidine hydrochloride to be nonirritating to eyes. Primary dermal irritation tests in guinea pigs using up to 5 times the proposed market concentration of detomidine hydrochloride on intact and abraded skin have demonstrated that the drug is nonirritating to skin and is apparently poorly absorbed dermally. However, in accordance with prudent clinical procedures, exposure of eyes or skin should be avoided and affected areas should be washed immediately if exposure does occur. As with all injectable drugs causing profound physiological effects, routine precautions should be employed by practitioners when handling and using loaded syringes to prevent accidental self-injection.

PRECAUTIONS

Before administration, careful consideration should be given to administering Dormosedan® to horses approaching or in endotoxic or traumatic shock, to horses with advanced liver or kidney disease, or to horses under stress from extreme heat, cold, fatigue, or high altitude. Protect treated horses from temperature extremes. Some horses, although apparently deeply sedated, may still respond to external stimuli. Routine safety measures should be employed to protect practitioners and handlers. Allowing the horse to stand quietly for 5 minutes before administration and for 10–15 minutes after injection may improve the response to Dormosedan®.

Dormosedan® is a potent α2-agonist, and extreme caution should be exercised in its use with other sedative or analgesic drugs for they may produce additive effects.

When using any analgesic to help alleviate abdominal pain, a complete physical examination and diagnostic work-up are necessary to determine the etiology of the pain.

Food and water should be withheld until the sedative effect of Dormosedan® has worn off.

ADVERSE REACTIONS

Occasional reports of anaphylactic-like reactions have been received, including 1 or more ofthe following: urticaria, skin plaques, dyspnea, edema of the upper airways, trembling, recumbency, and death. The use of epinephrine should be avoided since epinephrine may potentiate the effects of α2-agonists. Reports of mild adverse reactions have resolved uneventfully without treatment. Severe adverse reactions should be treated symptomatically. As with all α2-agonists, the potential for isolated cases of hypersensitivity exist, including paradoxical response (excitation).

CONTACT INFORMATION

For a copy of the Safety Data Sheet or to report adverse reactions, call Zoetis Inc. at 1-888-963-8471. For additional information about adverse drug experience reporting for animal drugs, contact FDA at 1-888-FDA-VETS or www.fda.gov/reportanimalae.

SIDE EFFECTS

Horses treated with Dormosedan® exhibit hypertension. Bradycardia routinely occurs 1 minute after injection. The relationship between hypertension and bradycardia is consistent with an adaptive baroreceptor response to the increased pressure and inconsistent with a primary drug-induced bradycardia. Piloerection, sweating, salivation, and slight muscle tremors are frequently seen after administration. Partial transient penis prolapse may be seen. Partial AV and SA blocks may occur with decreased heart and respiratory rates. Urination typically occurs during recovery at about 45–60 minutes posttreatment, depending on dosage. Incoordination or staggering is usually seen only during the first 3–5 minutes after injection, until animals have secured a firm footing.

Because of continued lowering of the head during sedation, mucus discharges from the nose and, occasionally, edema of the head and face may be seen. Holding the head in a slightly elevated position generally prevents these effects.

OVERDOSAGE

Detomidine hydrochloride is tolerated in horses at up to 200 mcg/kg of body weight (10 times the low dosage and 5 times the high dosage). In safety studies in horses, detomidine hydrochloride at 400 mcg/kg of body weight administered daily for 3 consecutive days produced microscopic foci of myocardial necrosis in 1 of 8 horses.

DOSAGE AND ADMINISTRATION:

For Sedation

Administer Dormosedan® IV or IM at the rates of 20 or 40 mcg detomidine hydrochloride per kg of body weight (0.2 or 0.4 mL of Dormosedan® per 100 kg or 220 lb), depending on the depth and duration of sedation required. Onset of sedative effects should be reached within 2–4 minutes after IV administration and 3–5 minutes after IM administration. Twenty mcg/kg will provide 30–90 minutes of sedation and 40 mcg/kg will provide approximately 90 minutes to 2 hours of sedation.

For Analgesia

Administer Dormosedan® IV at the rates of 20 or 40 mcg detomidine hydrochloride per kg of body weight (0.2 or 0.4 mL of Dormosedan® per 100 kg or 220 lb), depending on the depth and duration of analgesia required. Twenty mcg/kg will usually begin to take effect in 2–4 minutes and provide 30–45 minutes of analgesia. The 40 mcg/kg dose will also begin to take effect in 2–4 minutes and provide 45–75 minutes of analgesia.

For Both Sedation and Analgesia

Administer Dormosedan® IV at the rates of 20 or 40 mcg detomidine hydrochloride per kg of body weight (0.2 or 0.4 mL of Dormosedan® per 100 kg or 220 lb), depending on the depth and duration of sedation and analgesia required.

Before and after injection, the animal should be allowed to rest quietly.

STORAGE

Store at controlled room temperature 15°–30°C (59°–86°F) in the absence of light.

HOW SUPPLIED

Dormosedan® is supplied in 5- and 20-mL multidose vials.

Approved by FDA under NADA # 140-862
Manufactured by:
Orion Pharma
Orion Corporation
Espoo, Finland
zoetis
Distributed by:
Zoetis Inc.
Kalamazoo, MI 49007
Revised: September 2022
107224-11